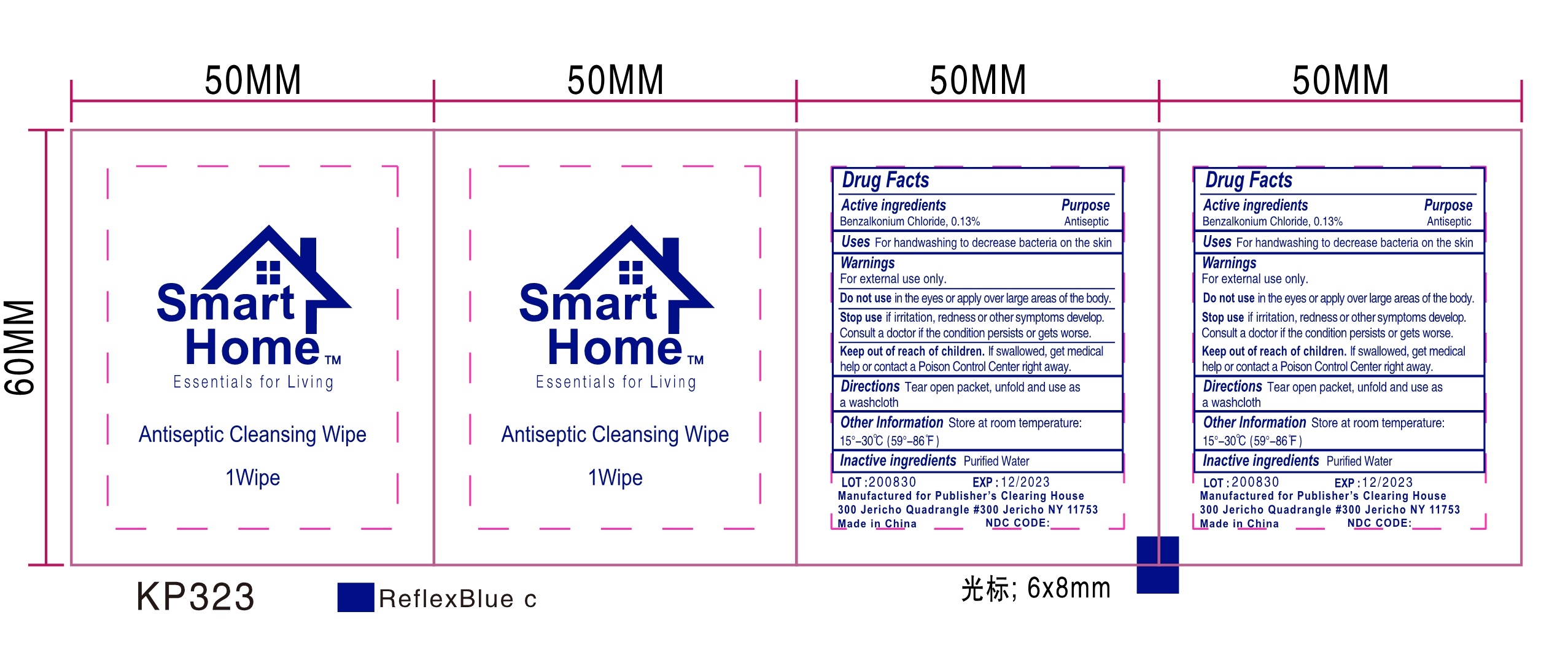 DRUG LABEL: Antiseptic Cleansing Wipe
NDC: 75427-014 | Form: CLOTH
Manufacturer: Jinhua City Wellmae Cosmetics Co., Ltd.
Category: otc | Type: HUMAN OTC DRUG LABEL
Date: 20220119

ACTIVE INGREDIENTS: BENZALKONIUM CHLORIDE 0.13 g/100 1
INACTIVE INGREDIENTS: WATER

75427-014
Antiseptic Cleansing Wipe

ACTIVE INGREDIENT

Benzalkonium Chloride 0.13%

Purpose

Antiseptic

Uses

For handwashing to decrease bacteria on the skin

WARNINGS

For external use only.

Do not use in the eyes or apply over large areas of the body.

Stop use if irritation, redness or other symptoms develop. Consult a doctor if the condition persists or gets worse.

Keep out of reach of children. lf swallowed, get medical help or contact a Poison Control Center right away.

Do not use in the eyes or apply over large areas of the body.

When using this product

Do not use in the eyes or apply over large areas of the body.

Stop use if irritation, redness or other symptoms develop. Consult a doctor if the condition persists or gets worse.

Keep out of reach of children. lf swallowed, get medical help or contact a Poison Control Center right away.

Stop use and ask a doctor

Stop use if irritation, redness or other symptoms develop. Consult a doctor if the condition persists or gets worse.

Keep out of reach of children. lf swallowed, get medical help or contact a Poison Control Center right away.

Directions

Tear open packet, unfold and use as a washcloth

Other Information

Store at room temperature:
15°-30℃ （59°-86℉）

Inactive Ingredients

Purified Water